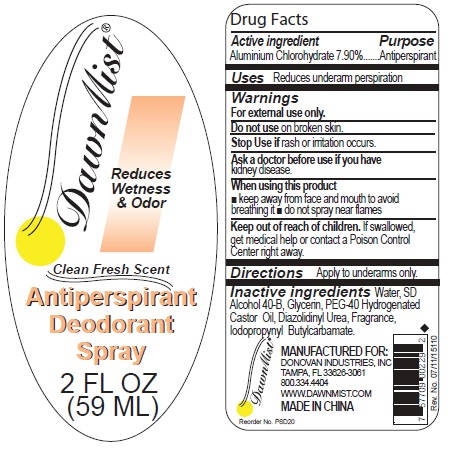 DRUG LABEL: DawnMist Antiperspirant and Deodorant
NDC: 55504-0230 | Form: SPRAY
Manufacturer: Donovan Industries, Inc.
Category: otc | Type: HUMAN OTC DRUG LABEL
Date: 20111005

ACTIVE INGREDIENTS: ALUMINUM CHLOROHYDRATE 7.90 mL/100 mL
INACTIVE INGREDIENTS: WATER; GLYCERIN; POLYOXYL 40 HYDROGENATED CASTOR OIL; DIAZOLIDINYL UREA; IODOPROPYNYL BUTYLCARBAMATE

DawnMist Antiperspirant Deodorant Spray

Active Ingredient

Aluminum Chlorohydrate 7.90%

Purpose

Antiperspirant

Uses

Reduces underarm perspiration

Warnings

For external use only

Do not use on broken skin.

Stop use if rash or irritation occurs

Ask a doctor before use if you have kidney disease

When using this product

- Keep away from face and mouth to avoid breathing it
- do not spray near flames

Keep out of reach of children.

If swallowed, get medical help or contact a Poison Control Center right away.

Directions

Apply to underarms only.

Inactive Ingredients

Water, SD Alcohol 40-B, Glycerin, PEG-40 Hydrogenated Castor Oil, Diazolidinyl Urea, Fragrance, Iodopropynyl Butylcarbamate

MANUFACTURED FOR:

DONOVAN INDUSTRIES, INC.
TAMPA, FL 33626-3061
800.334.4401
WWW.DAWNMIST.COM

MADE IN CHINA

PACKAGE LABEL

DawnMist

Reduces Wetness and Odor

Clean Fresh Scent

Antiperspirant

Deodorant

Spray